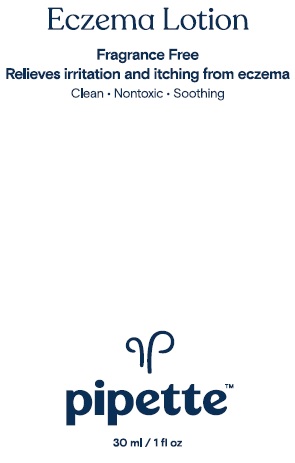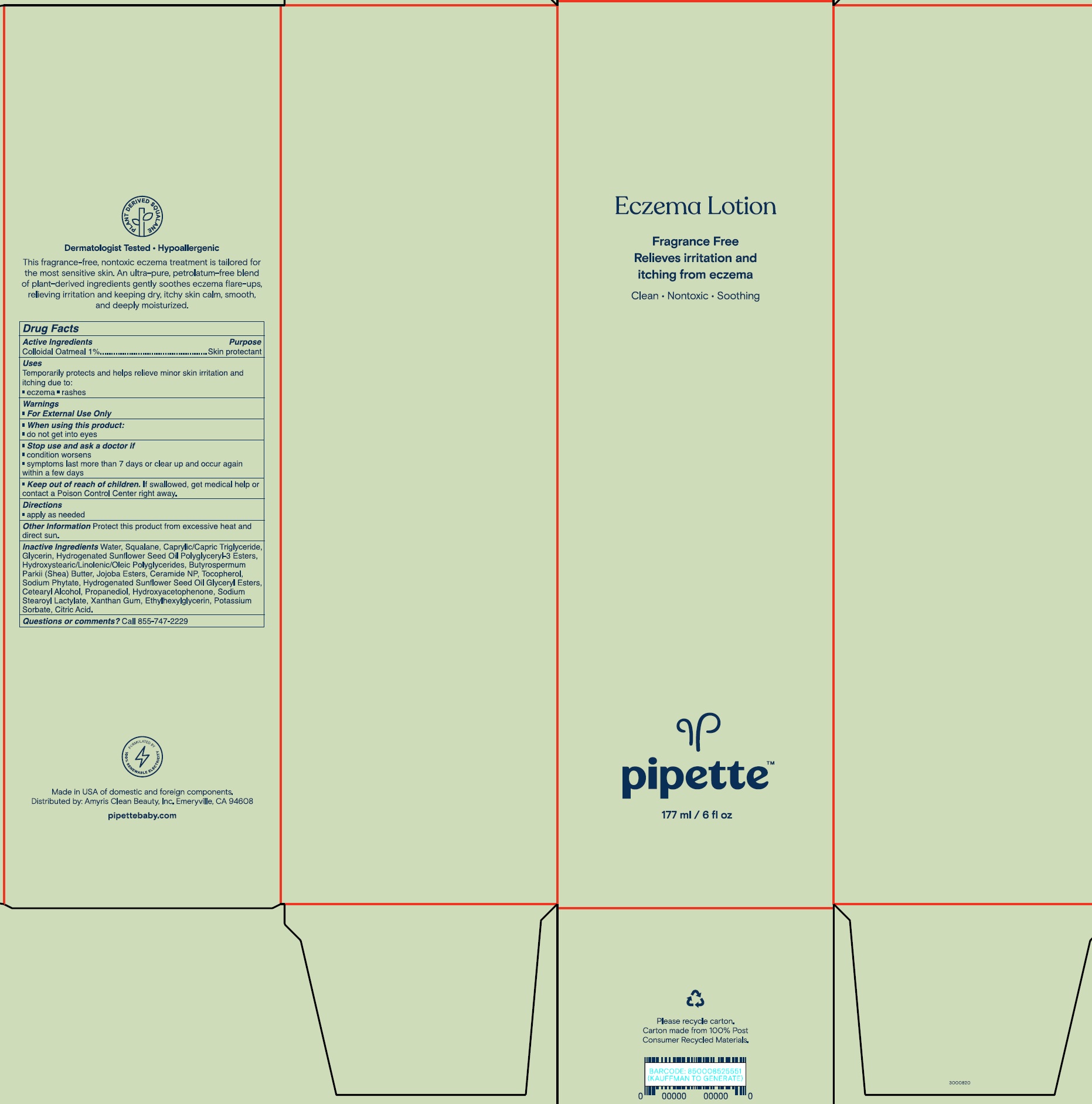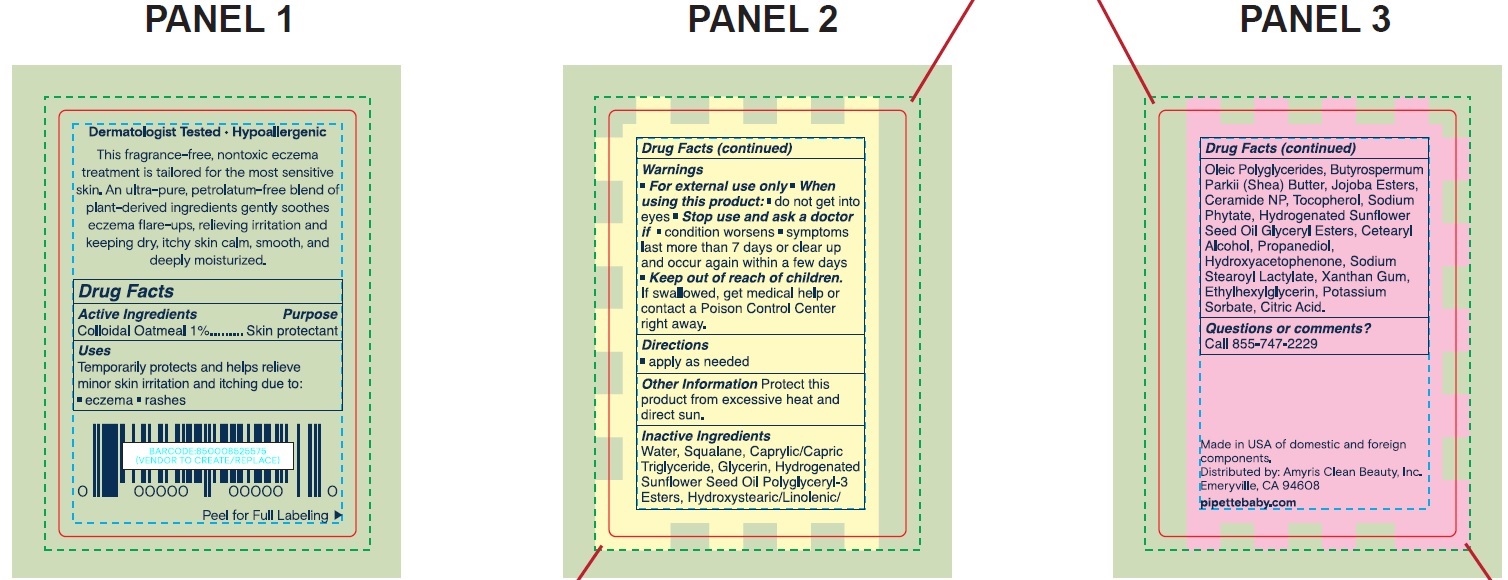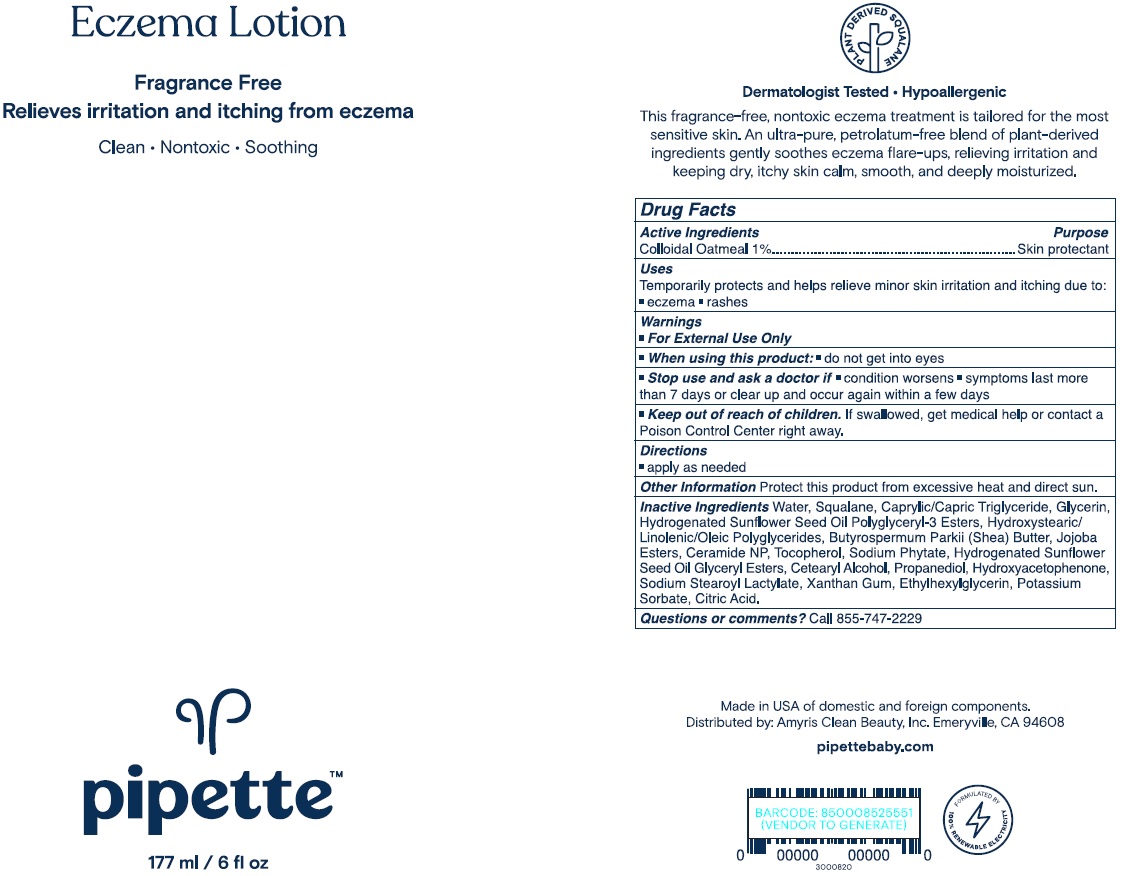 DRUG LABEL: Pipette Eczema
NDC: 73517-001 | Form: LIQUID
Manufacturer: Amyris, Inc
Category: otc | Type: HUMAN OTC DRUG LABEL
Date: 20220606

ACTIVE INGREDIENTS: OATMEAL 10 mg/1 mL
INACTIVE INGREDIENTS: WATER; SQUALANE; MEDIUM-CHAIN TRIGLYCERIDES; GLYCERIN; SHEA BUTTER; CERAMIDE NP; TOCOPHEROL; PHYTATE SODIUM; CETOSTEARYL ALCOHOL; PROPANEDIOL; HYDROXYACETOPHENONE; SODIUM STEAROYL LACTYLATE; XANTHAN GUM; ETHYLHEXYLGLYCERIN; POTASSIUM SORBATE; CITRIC ACID MONOHYDRATE

Pipette Eczema Lotion

Active Ingredients

Colloidal Oatmeal 1 %

Purpose

Skin protectant

Uses

Temporarily protects and helps relieve minor skin irritation and itching due to:

• eczema • rashes

Warnings

- For external use only

When using this product:

- do not get into eyes

Stop use and ask a doctor if

- condition worsens
- symptoms last more than 7 days or clear up and occur again within a few days

Keep out of reach of children.

- If swallowed, get medical help or contact a Poison Control Center right away.

Directions

- apply as needed

Other Information

Protect this product from excessive heat and direct sun.

Inactive Ingredients

Water, Squalane, Caprylic/Capric Triglyceride, Glycerin, Hydrogenated Sunflower Seed Oil Polyglyceryl-3 Esters, Hydroxystearic/Linolenic/Oleic Polyglycerides, Butyrospermum Parkii (Shea) Butter, Jojoba Esters, Ceramide NP, Tocopherol, Sodium Phytate, Hydrogenated Sunflower Seed Oil, Glyceryl Esters, Cetearyl Alcohol, Propanediol, Hydroxyacetophenone, Sodium Stearoyl Lactylate, Xanthan Gum, Ethylhexylglycerin, Potassium Sorbate, Citric Acid.

Questions or comments?

Call 855-747-2229

Package Labeling:73517-001-01

Add image transcription here...

Add image transcription here...